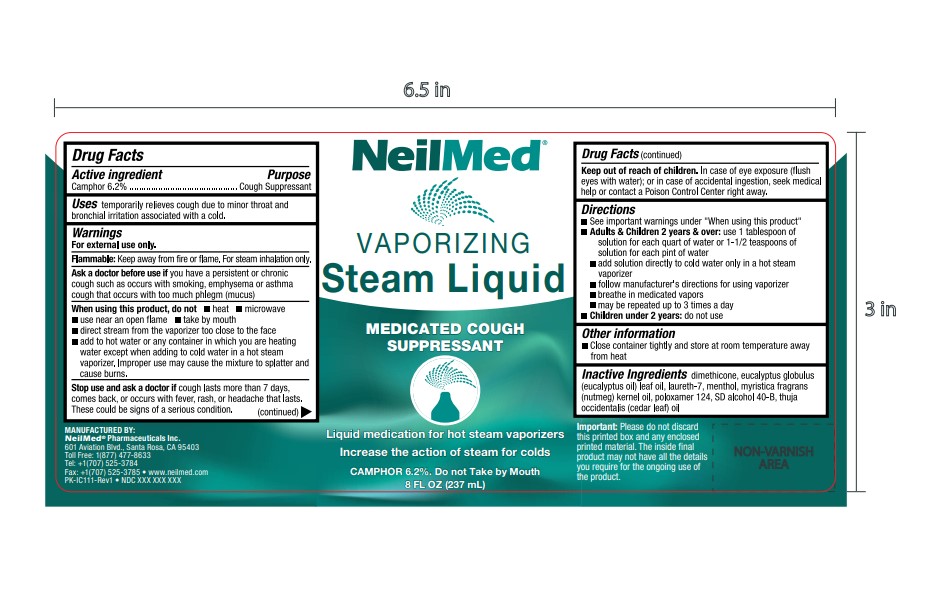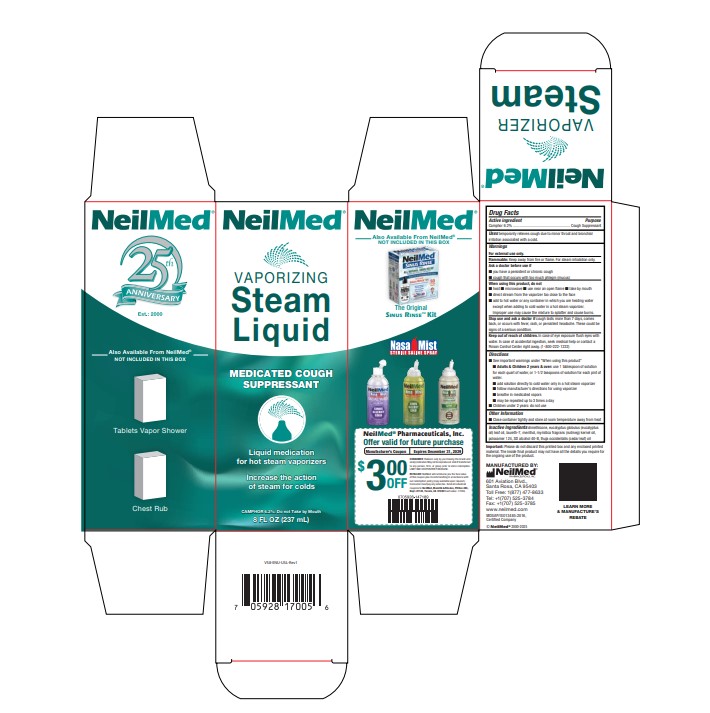 DRUG LABEL: Vaporizing Steam Liquid
NDC: 13709-332 | Form: SOLUTION
Manufacturer: NeilMed Pharmaceuticals Inc.
Category: otc | Type: HUMAN OTC DRUG LABEL
Date: 20250605

ACTIVE INGREDIENTS: CAMPHOR (SYNTHETIC) 62 mg/1 mL
INACTIVE INGREDIENTS: CEDAR LEAF OIL; ALCOHOL; DIMETHICONE; MENTHOL; EUCALYPTUS GLOBULUS LEAF; LAURETH-7; MYRISTICA FRAGRANS (NUTMEG) KERNEL OIL; POLOXAMER 124

Vaporizing steam liquid

Drug Facts

Camphor 6.2%

Purpose

Camphor 6.2%......................Cough Suppressant

Warnings

For External Use Only

Flammable: Keep away from fire or flame. For Steam Inhalation only.

Ask a doctor before use if

- you have a persistent or chronic cough
- cough that occurs with too much phlegm (mucus)

When using this product, do not

- Heat
- Microwave
- use near an open flame
- take by mouth
- direct stream from the vaporizer too close to the face
- add to hot water or any container in which you are heating water except when adding to cold water in a hot steam vaporizer. Improper use may cause the mixture to splatter and cause burns.

Stop use and ask a doctor if

cough lasts more than 7 days, comes back, or occurs with fever, rash, or persistent headache. These could be signs of a serious condition.

Keep out of reach of children

In case of eye exposure flush eyes with water. In case of accidental ingestion, seek medical help or contact a Poison Control Center right away. (1-800-222-1222)

Directions

- See important warnings under "When using this product"
- Adults & Children 2 years & over: use 1 tablespoon of solution for each quart of water, or 1-1/2 teaspoons of solution for each pint of water.
- add solution directly to cold water only in a hot steam vaporizer
- follow manufacturer's directions for using vaporizer
- breathe in medicated vapors
- may be repeated up to 3 times a day
- Children under 2 years: do not use

Other Information

- Close container tightly and store at room temperature away from heat

Important:

Please do not discard this printed box and any enclosed printed material. The inside final product may not have all the details you require for the ongoing use of the product

Directions

Adults & Children 2 years & over:

- use 1 tablespoon of solution for each quart of water or 1-1/2 teaspoons of solution for each pint of water.
- add solution directly to cold water only in a hot steam vaporizer.
- follow manufacturer's directions for using vaporizer
- breathe in medicated vapors
- may be repeated up to 3 times a day

Children under 2 years: do not use

Inactive Ingredients

dimethicone, eucalyptus(eucalyptus oil) leaf oil, laureth-7, menthol, myristica fragrans(nutmeg) kernel oil, poloxamer 124, SD alcohol 40-8, thuja occidentalis (cedar leaf) oil

Uses

Uses temporarily relieves cough due to minor throat and bronchial irritation associated with a cold.